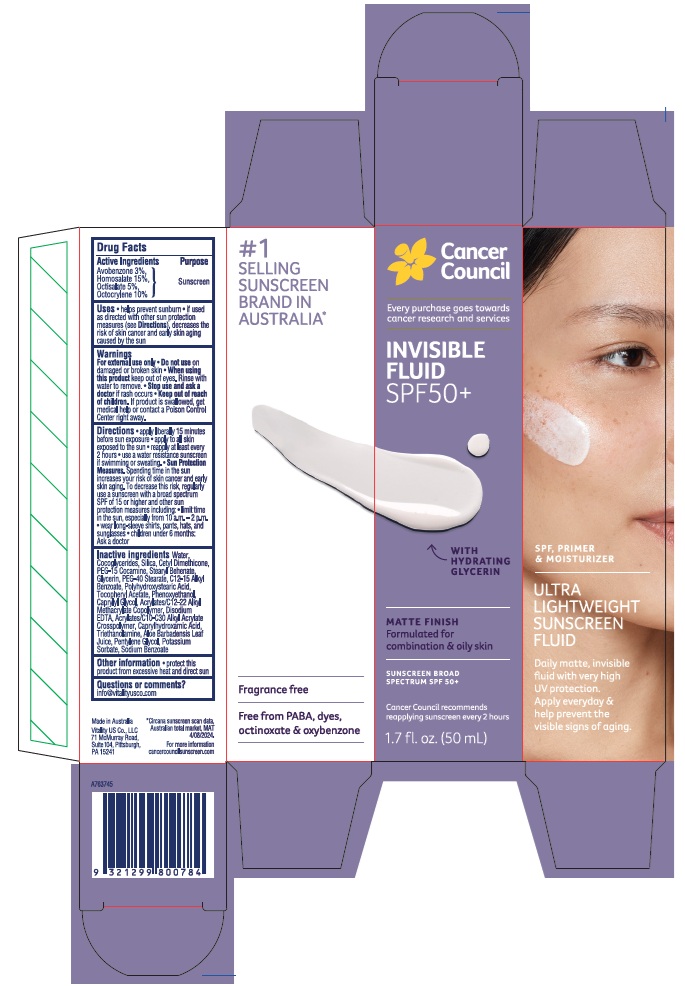 DRUG LABEL: Cancer Council Invisible Fluid SPF50 Plus
NDC: 84258-003 | Form: LOTION
Manufacturer: Vitality US Co.
Category: otc | Type: HUMAN OTC DRUG LABEL
Date: 20251203

ACTIVE INGREDIENTS: OCTISALATE 50 mg/1 mL; AVOBENZONE 30 mg/1 mL; HOMOSALATE 150 mg/1 mL; OCTOCRYLENE 100 mg/1 mL
INACTIVE INGREDIENTS: PEG-40 MONOSTEARATE; .ALPHA.-TOCOPHEROL ACETATE; STEARYL BEHENATE; GLYCERIN; ALKYL (C12-15) BENZOATE; PEG-15 COCAMINE; CETYL DIMETHICONE 45; WATER; POLYHYDROXYSTEARIC ACID (2300 MW); ALOE VERA LEAF; POLYOXYL 20 CETOSTEARYL ETHER; EDETATE DISODIUM; ACRYLATES/C10-30 ALKYL ACRYLATE CROSSPOLYMER (60000 MPA.S); PHENOXYETHANOL; CAPRYLHYDROXAMIC ACID; TROLAMINE; PENTYLENE GLYCOL; POTASSIUM SORBATE; SILICON DIOXIDE; SODIUM BENZOATE; COCO-GLYCERIDES; CAPRYLYL GLYCOL

Cancer Council Invisible Fluid SPF50 Plus

Active Ingredients

Avobenzone 3%

Homosalate 15%

Octisalate 5%

Octocrylene 10%

Purpose

Sunscreen

Uses

- helps prevent sunburn
- if used as directed with other sun protection measures (see Directions), decreases the risk of skin cancer and early skin aging caused by the sun

Warnings

For external use only

Do not use

on damaged or broken skin

When using this product

keep out of eyes. Rinse with water to remove.

Stop use and ask a doctor

if rash occurs

Keep out of reach of children.

If product is swallowed, get medical help or contact a Poison Control Center right away.

Directions

- apply liberally 15 minutes before sun exposure
- apply to all skin exposed to the sun
- reapply at least every 2 hours
- use a water resistance sunscreen if swimming or sweating.
- Sun Protection Measures. Spending time in the sun increases your risk of skin cancer and early skin aging. To decrease this risk, regularly use a sunscreen with a broad spectrum SPF of 15 or higher and other sun protection measures including:
- limit time in the sun, especially from 10 a.m. - 2 p.m.
- wear long-sleeve shirts, pants, hats, and sunglasses
- children under 6 months: Ask a doctor

Inactive ingredients

Water, Cocoglycerides, Silica, Cetyl Dimethicone, PEG-15 Cocamine, Stearyl Behenate, Glycerin, PEG-40 Stearate, C12-15 Alkyl Benzoate, Polyhydroxystearic Acid, Tocopheryl Acetate, Phenoxyethanol, Caprylyl Glycol, Acrylates/C12-22 Alkyl Methacrylate Copolymer, Disodium EDTA, Acrylates/C10-C30 Alkyl Acrylate Crosspolymer, Caprylhydroxamic Acid, Triethanolamine, Aloe Barbadensis Leaf Juice, Pentylene Glycol, Potassium Sorbate, Sodium Benzoate

Other information

- protect this product from excessive heat and direct sun

Questions or comments?

info@vitalityusco.com